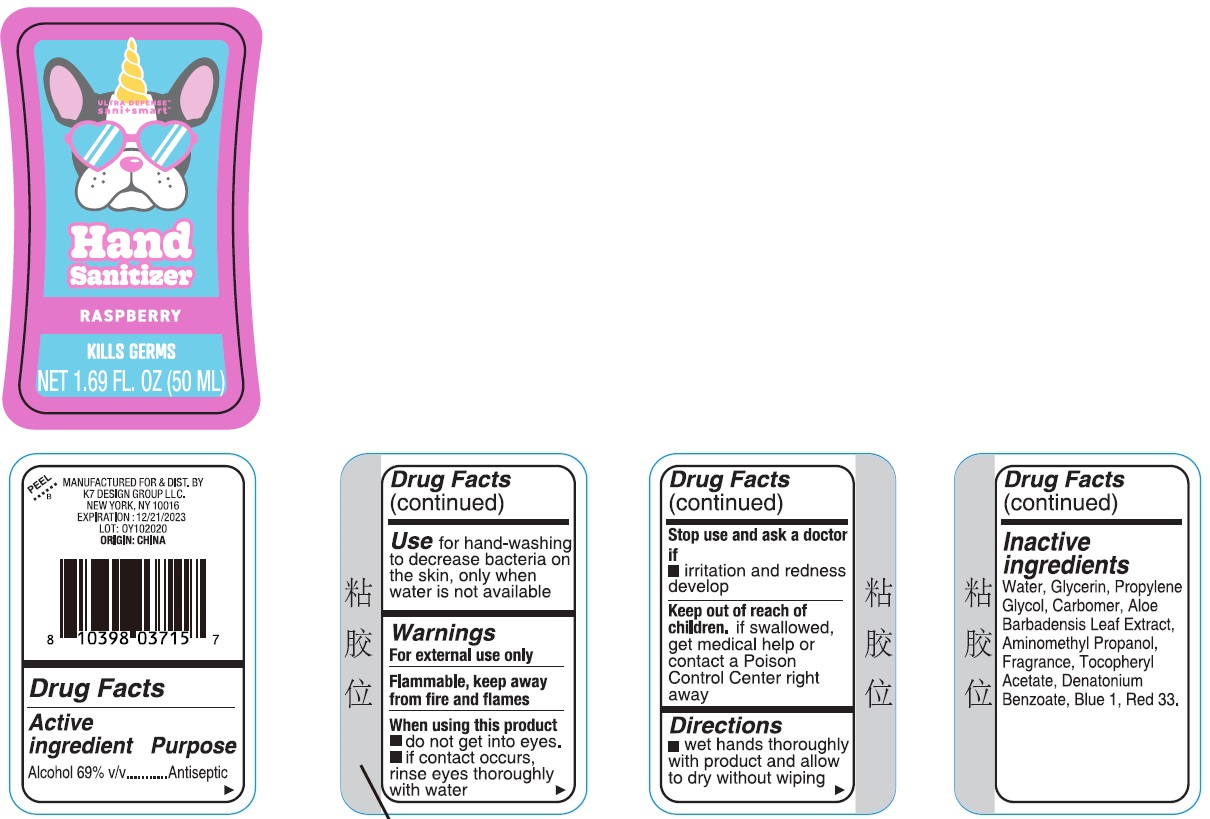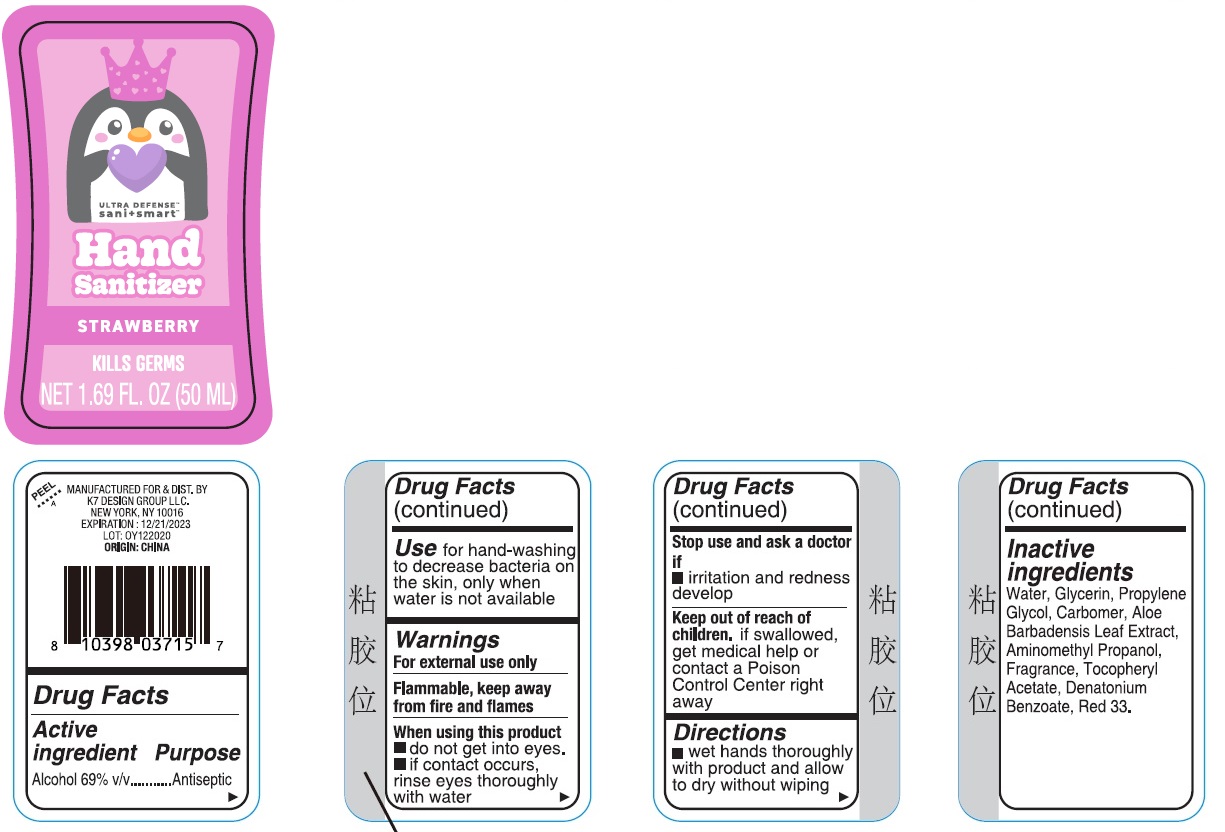 DRUG LABEL: Ultra Defense Sani Smart 2pk Hand Sanitizer
NDC: 74177-987 | Form: KIT | Route: TOPICAL
Manufacturer: K7 Design Group Inc.
Category: otc | Type: HUMAN OTC DRUG LABEL
Date: 20201124

ACTIVE INGREDIENTS: ALCOHOL 69 mL/100 mL; ALCOHOL 69 mL/100 mL
INACTIVE INGREDIENTS: WATER; AMINOMETHYLPROPANOL; .ALPHA.-TOCOPHEROL ACETATE; GLYCERIN; ALOE VERA LEAF; DENATONIUM BENZOATE; D&C RED NO. 33; PROPYLENE GLYCOL; CARBOMER HOMOPOLYMER, UNSPECIFIED TYPE; WATER; .ALPHA.-TOCOPHEROL ACETATE; GLYCERIN; ALOE VERA LEAF; DENATONIUM BENZOATE; D&C RED NO. 33; PROPYLENE GLYCOL; CARBOMER HOMOPOLYMER, UNSPECIFIED TYPE; AMINOMETHYLPROPANOL; FD&C BLUE NO. 1

Ultra Defense Sani Smart 2pk Hand Sanitizer

Active ingredient

Alcohol 69% v/v

Purpose

Antiseptic

Use

for hand-washing to decrease bacteria on the skin, only when water is not available

Warnings

For external use only

Flammable, keep away from fire and flames

When using this product

- do not get into eyes.
- if contact occurs, rinse eyes thoroughly with water

Stop use and ask a doctor if

- irritation and redness develop

Keep out of reach of children.

if swallowed, get medical help or contact a Poison Control Center right away

Directions

- wet hands thoroughly with product and allow to dry without wiping

Inactive ingredients

Raspberry

Water, Glycerin, Propylene Glycol, Carbomer, Aloe Barbadensis Leaf Extract, Aminomethyl Propanol, Fragrance, Tocopheryl Acetate, Denatonium Benzoate, Blue 1, Red 33.

Strawberry

Water, Glycerin, Propylene Glycol, Carbomer, Aloe Barbadensis Leaf Extract, Aminomethyl Propanol, Fragrance, Tocopheryl Acetate, Denatonium Benzoate, Red 33.

Company Information

MANUFACTURED FOR & DIST. BY K7 DESIGN GROUP LLC. NEW YORK, NY 10016

ORIGIN: CHINA